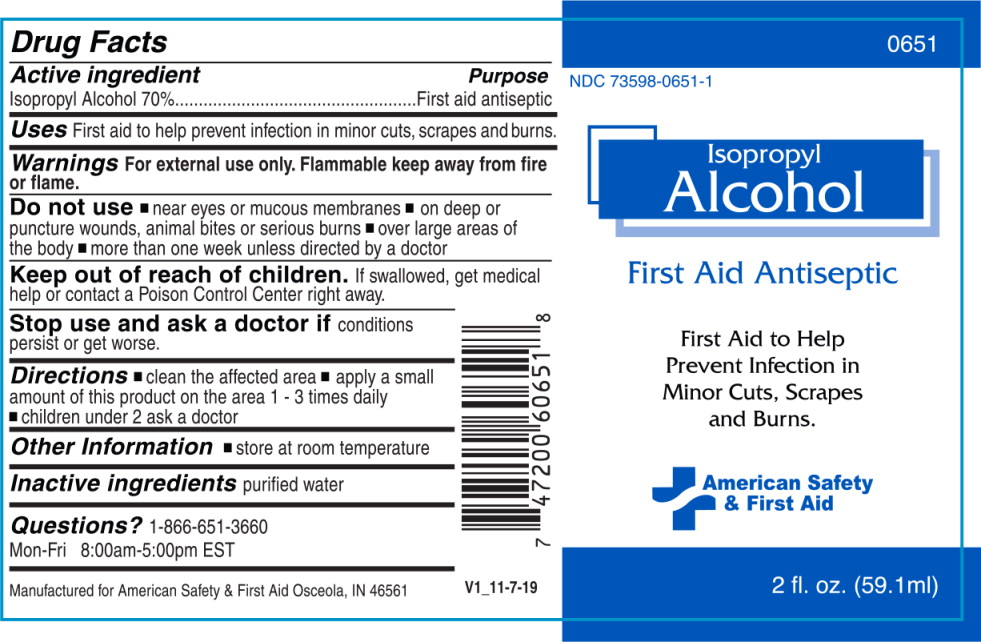 DRUG LABEL: Isopropyl Alcohol
NDC: 73598-0651 | Form: SPRAY
Manufacturer: JHK Inc
Category: otc | Type: HUMAN OTC DRUG LABEL
Date: 20240426

ACTIVE INGREDIENTS: Isopropyl Alcohol 700 mL/1 L
INACTIVE INGREDIENTS: water

Drug Facts

Active ingredient

Isopropyl Alcohol 70%

Purpose

First aid antiseptic

Uses

First aid to help prevent infection in minor cuts, scrapes and burns.

Warnings

For external use only. Flammable keep away from fire or flame.

Do not use

- near eyes or mucous membranes
- on deep or puncture wounds, animal bites or serious burns
- over large areas of the body
- more than one week unless directed by a doctor

Keep out of reach of children. If swallowed, get medical help or contact a Poison Control Center right away.

Stop use and ask a doctor if conditions persist or get worse.

Directions

- clean the affected area
- apply a small amount of this product on the area 1 - 3 times daily
- children under 2 ask a doctor

Other Information

- store at room temperature

Inactive Ingredients

purified water

Questions?

1-866-651-3660

Mon-Fri 8:00am-5:00pm EST

Manufactured for American Safety & First Aid Osceola, IN 46561

Principal Display Panel – Bottle Label

0651

NDC 73598-0651-1

Isopropyl
Alcohol

First Aid Antiseptic

First Aid to Help
Prevent Infection in
Minor Cuts, Scrapes
and Burns.

American Safety
& First Aid

2 fl. Oz. (59.1 ml)